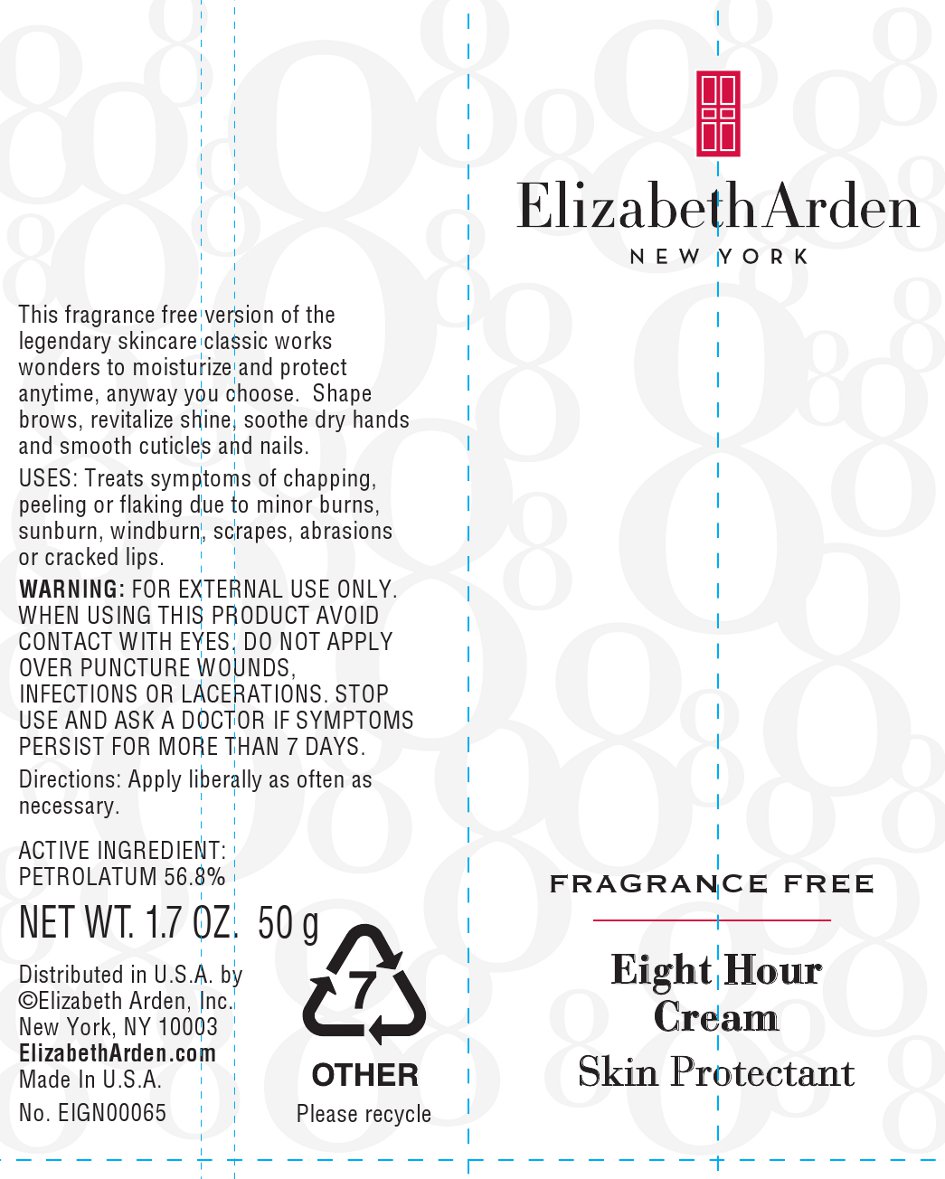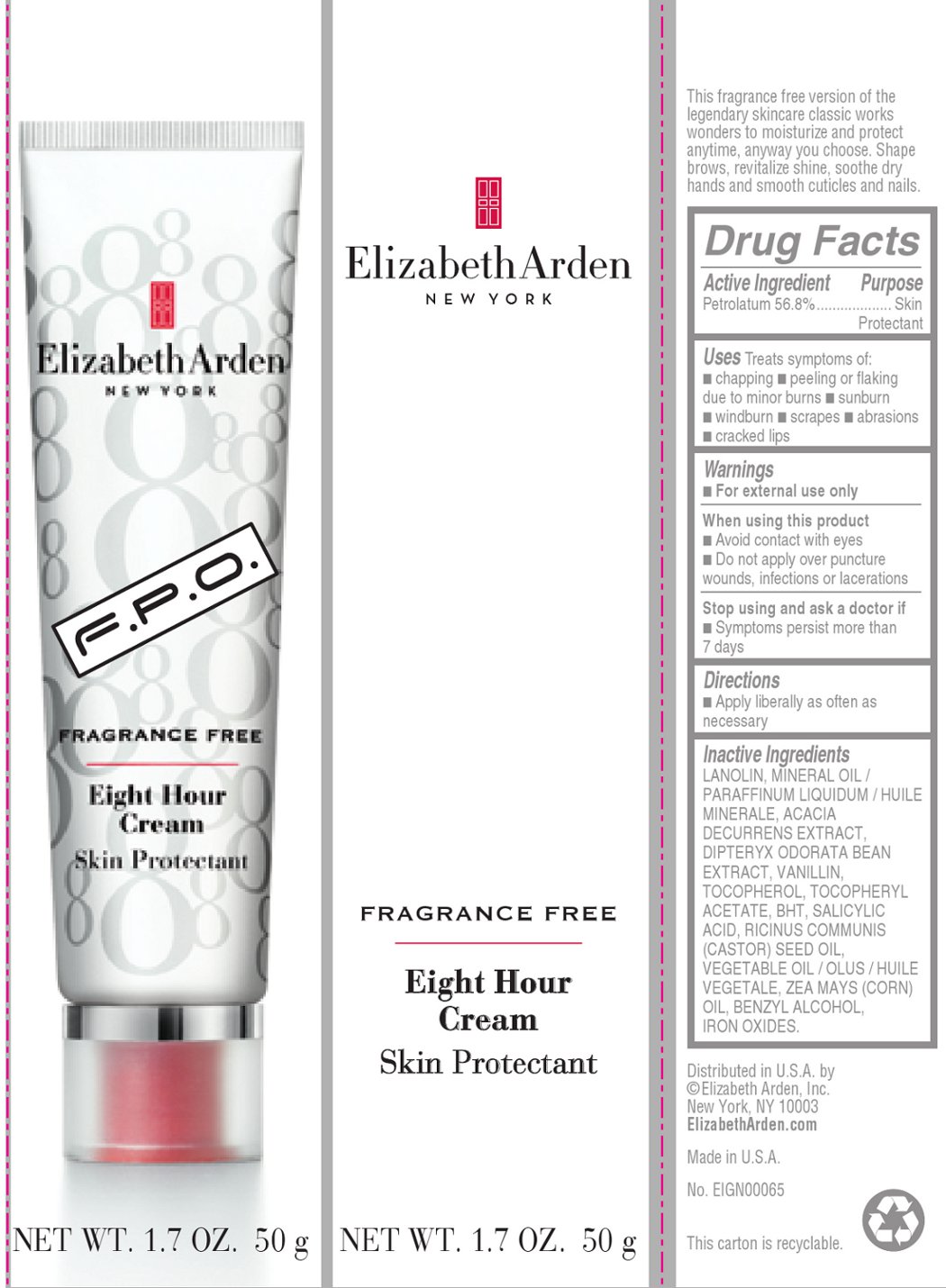 DRUG LABEL: EIGHT HOUR CREAM SKIN PROTECTANT FRAGRANCE FREE
NDC: 67938-1149 | Form: CREAM
Manufacturer: Elizabeth Arden, Inc
Category: otc | Type: HUMAN OTC DRUG LABEL
Date: 20111004

ACTIVE INGREDIENTS: PETROLATUM 28.4 g/50 g
INACTIVE INGREDIENTS: LANOLIN; MINERAL OIL; VANILLIN; SALICYLIC ACID

BC1149

DESCRIPTION

This fragrance free version of the legendary skincare classic works wonders to moisturize and protect anytime, anyway you choose. Shape brows, revitalize shine, soothe dry hands and smooth cuticles and nails.

INDICATIONS AND USAGE

To use: Apply liberally as often as necessary.

WARNINGS

Warnings: For external use only. When using this product avoid contact with eyes. Do not apply over puncture wounds, infections or lacerations. Stop using and ask a doctor if symptoms persists more than 7 days.

OTC - ACTIVE INGREDIENT

Active Ingredient: Petrolatum 56.8%

INACTIVE INGREDIENT

LANOLIN, MINERAL OIL/PARAFFINUM LIQUIDUM/HUILE MINÉRALE, ACACIA DECURRENS EXTRACT, DIPTERYX ODORATA BEAN EXTRACT, VANILLIN, TOCOPHEROL, TOCOPHERYL ACETATE, BHT, SALICYLIC ACID, RICINUS COMMUNIS (CASTOR) SEED OIL, VEGETABLE OIL/OLUS/HUILE VÉGÉTALE, ZEA MAYS (CORN) OIL, BENZYL ALCOHOL, IRON OXIDES.

DOSAGE & ADMINISTRATION

Apply liberally.

OTC - KEEP OUT OF REACH OF CHILDREN

Keep out of reach of children.

OTC - PURPOSE

Skin protectant.

OTC - WHEN USING

Avoid contact with eyes. Do not apply over puncture wounds, infections or lacerations.